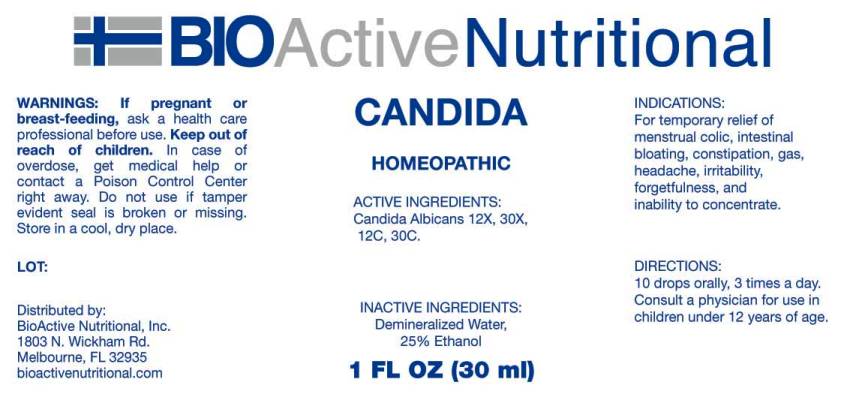 DRUG LABEL: Candida
NDC: 43857-0177 | Form: LIQUID
Manufacturer: BioActive Nutritional, Inc.
Category: homeopathic | Type: HUMAN OTC DRUG LABEL
Date: 20170215

ACTIVE INGREDIENTS: CANDIDA ALBICANS 12 [hp_X]/1 mL
INACTIVE INGREDIENTS: WATER; ALCOHOL

Drug Facts:

ACTIVE INGREDIENTS:

Candida Albicans 12X, 30X, 12C, 30C.

INDICATIONS:

For temporary relief of menstrual colic, intestinal bloating, constipation, gas, headache, irritability, forgetfulness, and inability to concentrate.

WARNINGS:

If pregnant or breast-feeding, ask a health care professional before use.

Keep out of reach of children. In case of overdose, get medical help or contact a Poison Control Center right away.

Do not use if tamper evident seal is broken or missing.

Store in a cool, dry place.

Keep out of reach of children. In case of overdose, get medical help or contact a Poison Control Center right away.

DIRECTIONS:

10 drops orally, 3 times a day. Consult a physician for use in children under 12 years of age.

INDICATIONS:

For temporary relief of menstrual colic, intestinal bloating, constipation, gas, headache, irritability, forgetfulness, and inability to concentrate.

INACTIVE INGREDIENTS:

Demineralized Water, 25% Ethanol

QUESTIONS:

Distributed by:
BioActive Nutritional, Inc.
1803 N. Wickham Rd.
Melbourne, FL 32935
bioactivenutritional.com

PACKAGE LABEL DISPLAY:

BIOActive Nutritional

CANDIDA

HOMEOPATHIC

1 FL OZ (30 ml)